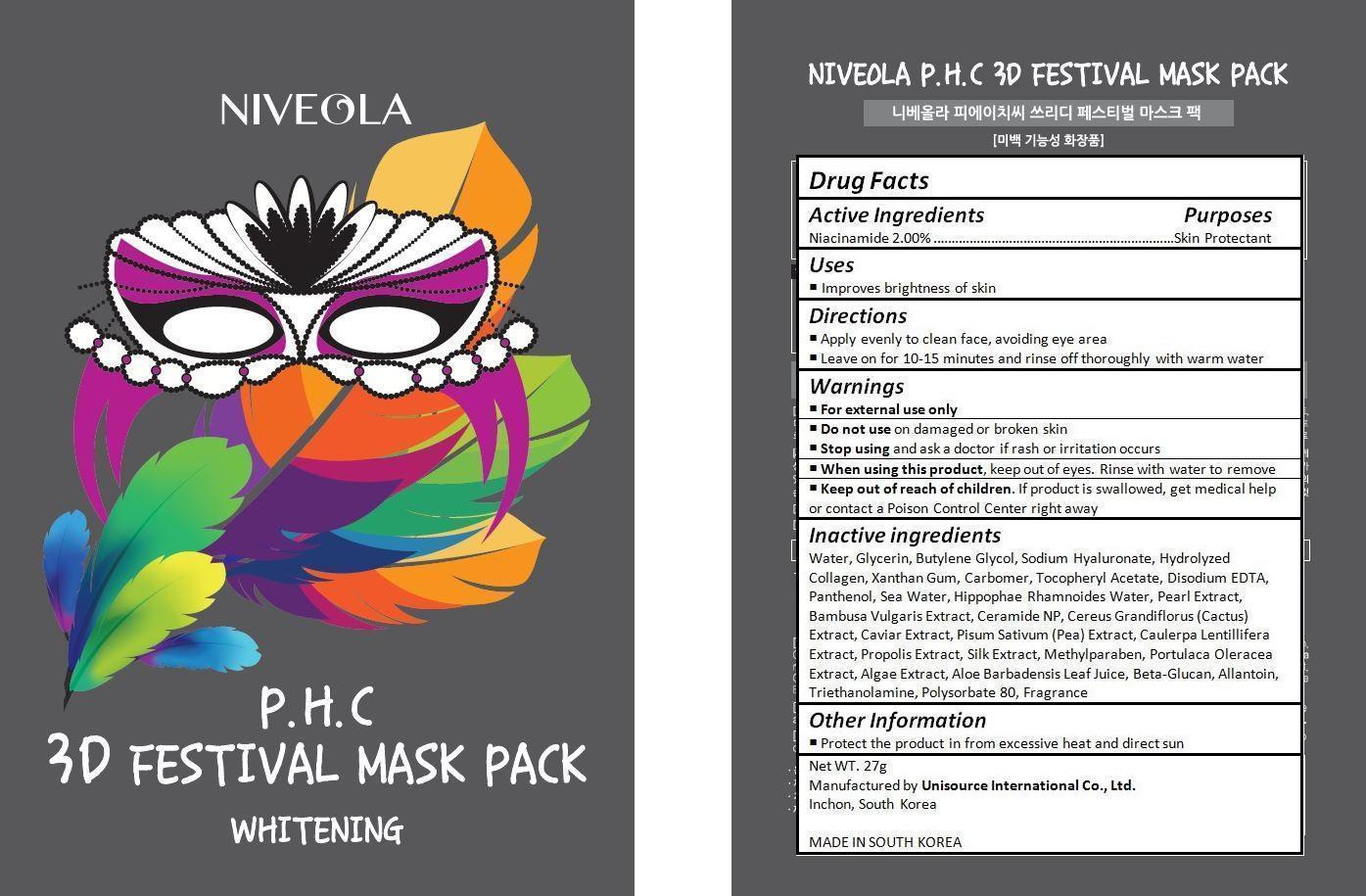 DRUG LABEL: NIVEOLA P.H.C 3D FESTIVAL MASK PACK
NDC: 70133-003 | Form: CREAM
Manufacturer: Unisource International Co., Ltd.
Category: otc | Type: HUMAN OTC DRUG LABEL
Date: 20151008

ACTIVE INGREDIENTS: Niacinamide 0.54 g/27 g
INACTIVE INGREDIENTS: WATER; GLYCERIN; BUTYLENE GLYCOL; HYALURONATE SODIUM; XANTHAN GUM; CARBOMER HOMOPOLYMER TYPE C (ALLYL PENTAERYTHRITOL CROSSLINKED); .ALPHA.-TOCOPHEROL ACETATE; EDETATE DISODIUM; PANTHENOL; SODIUM CHLORIDE; HIPPOPHAE RHAMNOIDES WHOLE; PEARL (HYRIOPSIS CUMINGII); BAMBUSA VULGARIS TOP; CERAMIDE NP; SELENICEREUS GRANDIFLORUS WHOLE; CAVIAR, UNSPECIFIED; PEA; CAULERPA LENTILLIFERA; PROPOLIS WAX; BOMBYX MORI FIBER; METHYLPARABEN; PURSLANE; ALOE VERA LEAF; CURDLAN; ALLANTOIN; TROLAMINE; POLYSORBATE 80

Drug Facts

ACTIVE INGREDIENT

Niacinamide 2.00%

PURPOSE

Skin Protectant

INDICATIONS AND USAGE

Improves brightness of skin

DOSAGE AND ADMINISTRATION

Apply evenly to clean face, avoiding eye area
Leave on for 10-15 minutes and rinse off thoroughly with warm water

WARNINGS

For external use only.
Do not use on damaged or broken skin.
When using this product, keep out of eyes. Rinse with water to remove.
Stop using and ask a doctor if rash occurs.

KEEP OUT OF REACH OF CHILDREN

Keep out of reach of the children. If product is swallowed, get medical help or contact a poison control center right away.

INACTIVE INGREDIENT

Water, Glycerin, Butylene Glycol, Sodium Hyaluronate, Hydrolyzed Collagen, Xanthan Gum, Carbomer, Tocopheryl Acetate, Disodium EDTA, Panthenol, Sea Water, Hippophae Rhamnoides Water, Pearl Extract, Bambusa Vulgaris Extract, Ceramide NP, Cereus Grandiflorus (Cactus) Extract, Caviar Extract, Pisum Sativum (Pea) Extract, Caulerpa Lentillifera Extract, Propolis Extract, Silk Extract, Methylparaben, Portulaca Oleracea Extract, Algae Extract, Aloe Barbadensis Leaf Juice, Beta-Glucan, Allantoin, Triethanolamine, Polysorbate 80, Fragrance